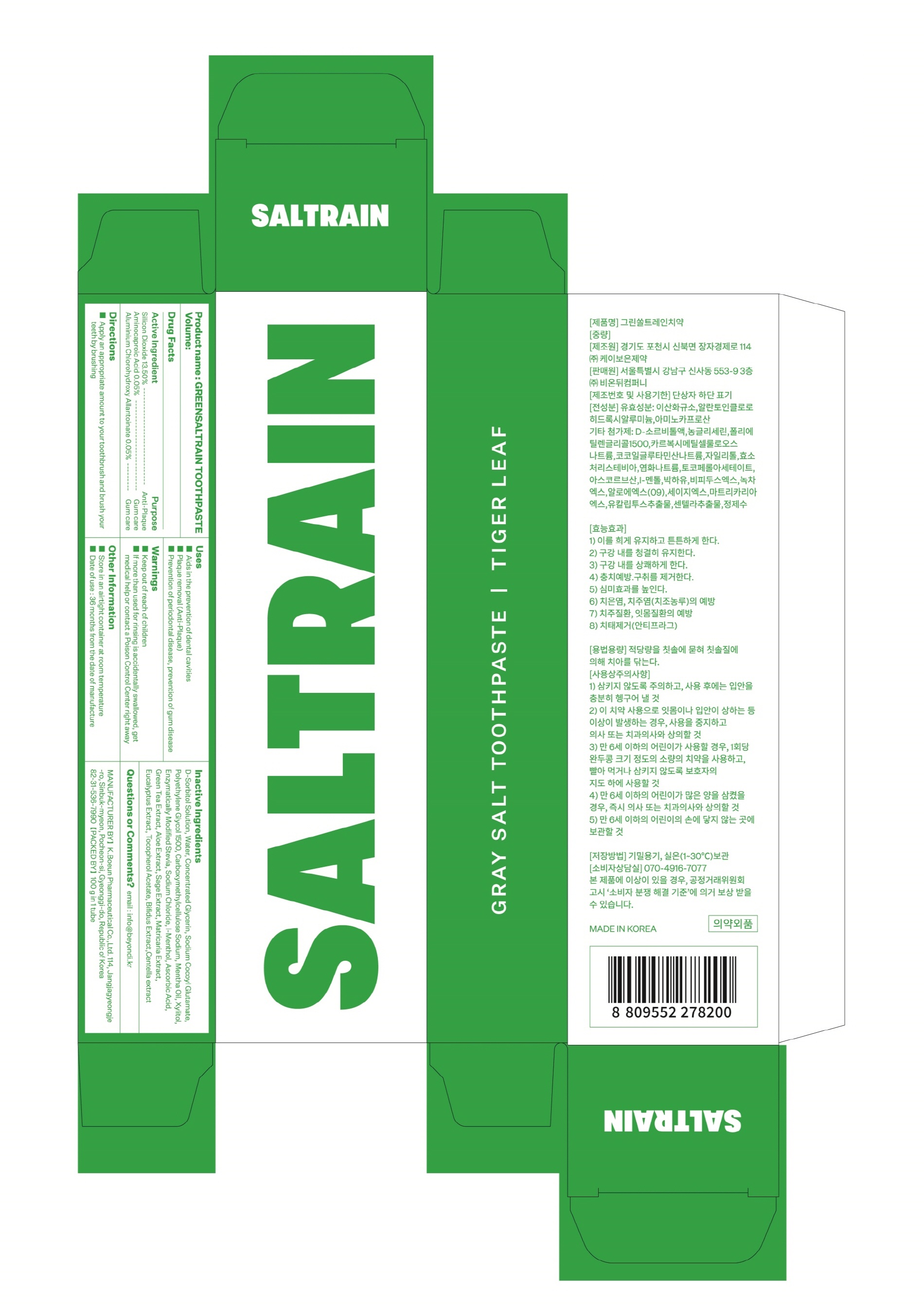 DRUG LABEL: GREENSALTRAIN TOOTH
NDC: 74724-0030 | Form: PASTE, DENTIFRICE
Manufacturer: K.Boeun Pharmaceutical Co.,Ltd.
Category: otc | Type: HUMAN OTC DRUG LABEL
Date: 20211130

ACTIVE INGREDIENTS: ALCLOXA 0.05 g/100 g; SILICON DIOXIDE 13.5 g/100 g; AMINOCAPROIC ACID 0.05 g/100 g
INACTIVE INGREDIENTS: XYLITOL; WATER

ACTIVE INGREDIENT

Silicon Dioxide, Aluminium Chlorohydroxy Allantoinate, Aminocaproic Acid

INACTIVE INGREDIENT

D-Sorbitol Solution
Concentrated Glycerin
Polyethylene Glycol 1500
Carboxymethylcellulose Sodium
Sodium Cocoyl Glutamate
Xylitol
Enzymatically Modified Stevia

Sodium Chloride
Tocopherol Acetate
Ascorbic Acid

l-Menthol
Mentha Oil

Bifidus Extract
Green Tea Extract

Aloe Extract

Sage Extract

Matricaria Extract

Eucalyptus Extract
Centella extract
Water

PURPOSE

For dental care

Keep out of reach of children

INDICATIONS AND USAGE

Apply an appropriate amount to your toothbrush and brush your teeth by brushing.

Warnings

Keep out of reach of children

■ If more than used for rinsing is accidentally swallowed, get medical help or contact a Poison Control Center right away.

Other Information

■ Store in an airtight container at room temperature

■ Date of use : 36 months from the date of manufacture

DOSAGE AND ADMINISTRATION

For dental use only